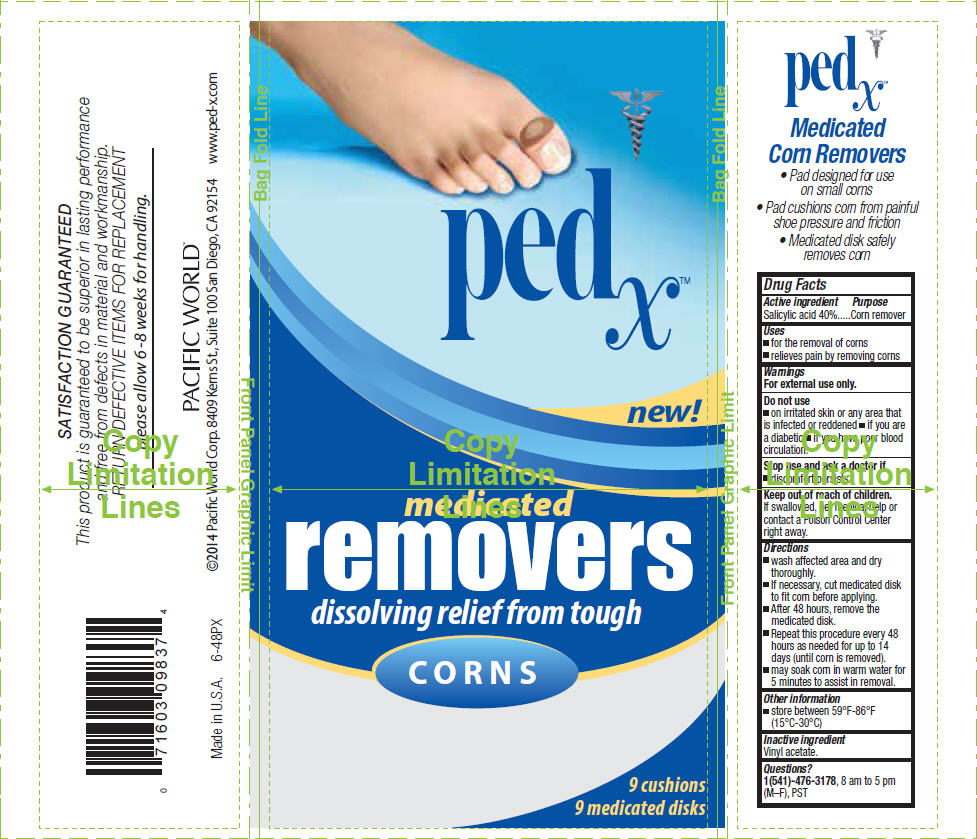 DRUG LABEL: Ped X Corn Removers, Medicated
NDC: 60193-402 | Form: PATCH
Manufacturer: Pacific World Corporation
Category: otc | Type: HUMAN OTC DRUG LABEL
Date: 20141017

ACTIVE INGREDIENTS: Salicylic acid 4 mg/1 1
INACTIVE INGREDIENTS: Vinyl acetate

Ped X™ Corn Removers, Medicated

Drug Facts

Active ingredient

Salicylic acid 40%

Purpose

Corn remover

Uses

- for the removal of corns
- relieves pain by removing corns

Warnings

For external use only.

Do not use

- on irritated skin or any area that is infected or reddened
- if you are a diabetic
- if you have poor blood circulation.

Stop use and ask a doctor if

- discomfort persists.

Keep out of reach of children.

If swallowed, get medical help or contact a Poison Control Center right away.

Directions

- wash affected area and dry thoroughly.
- If necessary, cut medicated disk to fit corn before applying.
- After 48 hours, remove the medicated disk.
- Repeat this procedure every 48 hours as needed for up to 14 days (until corn is removed).
- may soak corn in warm water for 5 minutes to assist in removal.

Other information

- store between 59°F-86°F (15°C-30°C)

Inactive ingredient

Vinyl acetate.

Questions?

1(541)-476-3178, 8 am to 5 pm (M–F), PST

PRINCIPAL DISPLAY PANEL - 9 Disk Cello Pack

pedx™

new!

medicated
removers
dissolving relief from tough

CORNS

9 cushions
9 medicated disks